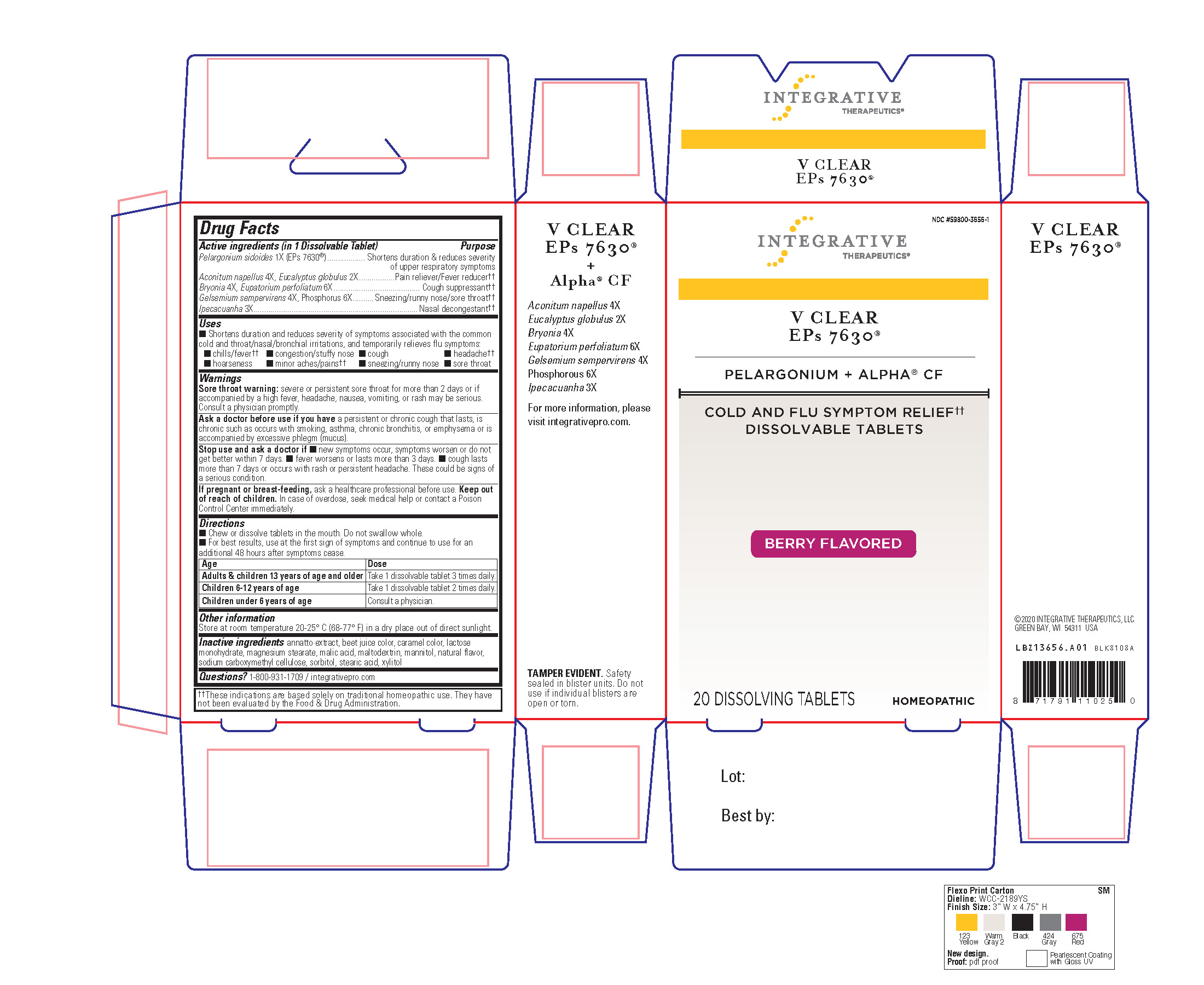 DRUG LABEL: vClear Berry Dissolving Tablets
NDC: 59800-3656 | Form: TABLET, CHEWABLE
Manufacturer: Schwabe North America, Inc.
Category: homeopathic | Type: HUMAN OTC DRUG LABEL
Date: 20251208

ACTIVE INGREDIENTS: PELARGONIUM SIDOIDES ROOT 1 [hp_X]/1 1; ACONITUM NAPELLUS 4 [hp_X]/1 1; BRYONIA ALBA ROOT 4 [hp_X]/1 1; EUCALYPTUS GLOBULUS LEAF 2 [hp_X]/1 1; EUPATORIUM PERFOLIATUM FLOWERING TOP 6 [hp_X]/1 1; GELSEMIUM SEMPERVIRENS ROOT 4 [hp_X]/1 1; IPECAC 3 [hp_X]/1 1; PHOSPHORUS 6 [hp_X]/1 1
INACTIVE INGREDIENTS: ANNATTO; BEET JUICE; CARAMEL; LACTOSE MONOHYDRATE; MAGNESIUM STEARATE; MALIC ACID; MALTODEXTRIN; MANNITOL; CROSCARMELLOSE SODIUM; SORBITOL; STEARIC ACID; XYLITOL

vClear Berry Dissolving tabs

Active Ingredient

PELARGONIUM SIDOIDES 1X

ACONITUM NAPELLUS 4X

EUCALYPTUS GLOBULUS 2X

BRYONIA 4X

EUPATORIUM PERFOLIATUM 6X

GELSEMIUM SEMPERVIRENS 4X

PHOSPHORUS 6X

IPECACUANHA 3X

Inactive Ingredient

ANNATTO EXRACT

BEET JUICE COLOR

CARAMEL COLOR

LACTOSE MONOHYDRATE

MAGNESIUM STEARATE

MALIC ACID

MALTODEXTRIN

MANNITOL

NATURAL FLAVOR

SODIUM CARBOXYMETHYL CELLULOSE

SORBITOL

STEARIC ACID

XYLITOL

Dosage & Administration

Directions

Chew or dissolve tablets in the mouth. Do not swallow whole.

For best results, use at first sign of symptoms and continue to use for an additional 48 hours after symptoms cease.
Adults & children 13 years of age and older: Take 1 dissolvable tablet 3 times daily.

Children 6-12 years of age: Take 1 dissolvable tablet 2 times daily.

Children under 6 years of age: Consult a physician.

Indications & Usage

Shortens duration and reduces severity of symptoms associated with the common cold and throat/nasal/bronchial irritations, and temporarily relieves flu symptoms: chills/fever, congestion/stuffy nose, cough, headache, hoarseness, minor aches/pains, sneezing/runny nose, sore throat.

Purpose

Shortens duration and reduces severity of symptoms associated with the common cold and throat/nasal/bronchial irritations, and temporarily relieves flu symptoms: chills/fever, congestion/stuffy nose, cough, headache, hoarseness, minor aches/pains, sneezing/runny nose, sore throat.

Warnings

Sore throat warning: severe or persistent sore throat for more than 2 days or if accompanied by a high fever, headache, nausea, vomiting or rash may be serious.

Consult a physician promptly.

Ask Doctor

Ask a doctor before use if you have a persistent or chronic cough that lasts, is chronic such as occurs with smoking, asthma, chronic bronchitis or emphysema, or is accompanied by excessive phlegm (mucus).

Stop Use

Stop use and ask a doctor if new symptoms occur, symptoms worsen or do not get better within 7 days, fever worsens or lasts more than 3 days, cough lasts more than days or occurs with rash or persistant headache.

These could be signs of a serious condition.

Pregnancy or Breast Feeding

If pregnant or breast-feeding, ask a healthcare professional before use.

Keep out reach of children

Keep out of reach of chidlren.

Overdosage

In case of overdose, seek medical help or contact a Poison Control Center immediately.